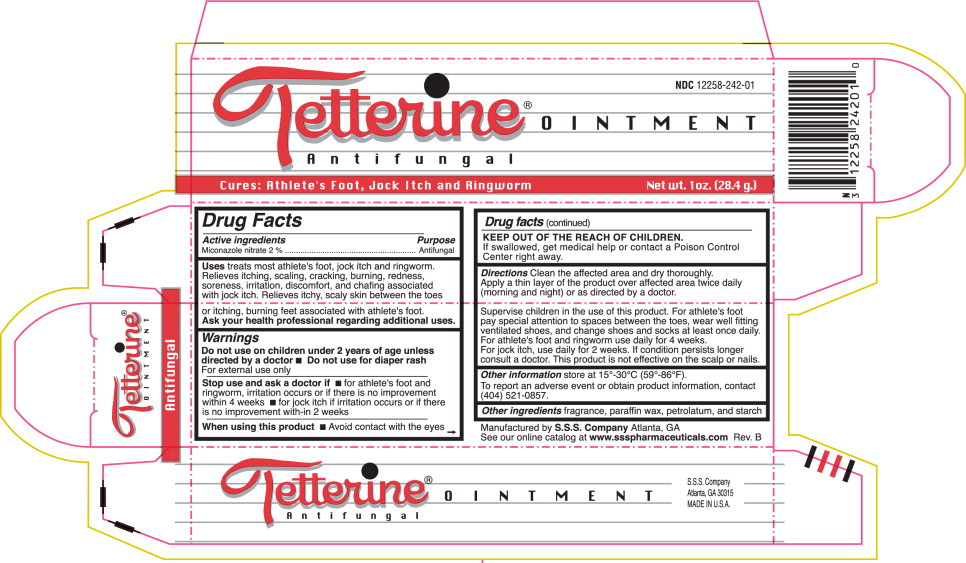 DRUG LABEL: White Tetterine
NDC: 12258-242 | Form: OINTMENT
Manufacturer: S.S.S. Company
Category: otc | Type: HUMAN OTC DRUG LABEL
Date: 20260108

ACTIVE INGREDIENTS: MICONAZOLE NITRATE 2 g/100 g
INACTIVE INGREDIENTS: PETROLATUM; ALUMINUM STARCH OCTENYLSUCCINATE; PARAFFIN

DRUG FACTS

Active Ingredient:

Miconazole Nitrate 2%

Purpose:

Antifungal

Uses

treats most athlete's foot, jock itch and ringworm. Relieves itching, scaling, cracking, burning, redness, soreness, irritation, discomfort, and chafing associated with jock itch. Relieves itchy, scaly skin between the toes or itching, burning feet associated with athlete's foot

Ask your health professional regarding additional uses

Warnings

Do not use on children under 2 years of age unless directed by a doctor

- Do not use on diaper rash

For external use only

Stop use and ask a doctor if

- for athlete's foot and ringworm, irritation occurs or if there is no improvement within 4 weeks
- for jock itch if irritation occurs of if there is no improvement with-in 2 weeks

When using this product

- Avoid contact with eyes

KEEP OUT OF REACH OF CHILDREN

If swallowed, get medical help or contact a Poison Control Center right away

Directions

Clean the affected area and dry thoroughly. Apply a thin layer of the product over the affected area twice daily (morning and night) or as directed by a doctor.

Supervise children in the use of this product. For athlete's foot pay special attention to the spaces between the toes, wear well fitting ventilated shoes, and change shoes and socks at least once daily. For athlete's foot and ringworm use daily for 4 weeks. For jock itch, use daily for 2 weeks. If condition persists longer consult a doctor. This product is not effective on the scalp or nails.

Other Information

store at 15°-30°C (59°-86°F).

To report an adverse event or obtain product information, contact (404) 521-0857.

Other Ingredients

Fragrance, paraffin wax, petrolatum, and starch

Principal Display Panel

NDC 12258-242-01

Tetterine® OINTMENT

Antifungal

Cures: Athlete's Foot, Jock Itch and Ringworm

Net wt. 1oz. (28.4 g.)

Other Packaging Content

S.S.S. Company

Atlanta, GA 30315

MADE IN U.S.A.

Manufactured by S.S.S. Company Atlanta, GA

See our online catalog at www.ssspharmaceuticals.com Rev. B